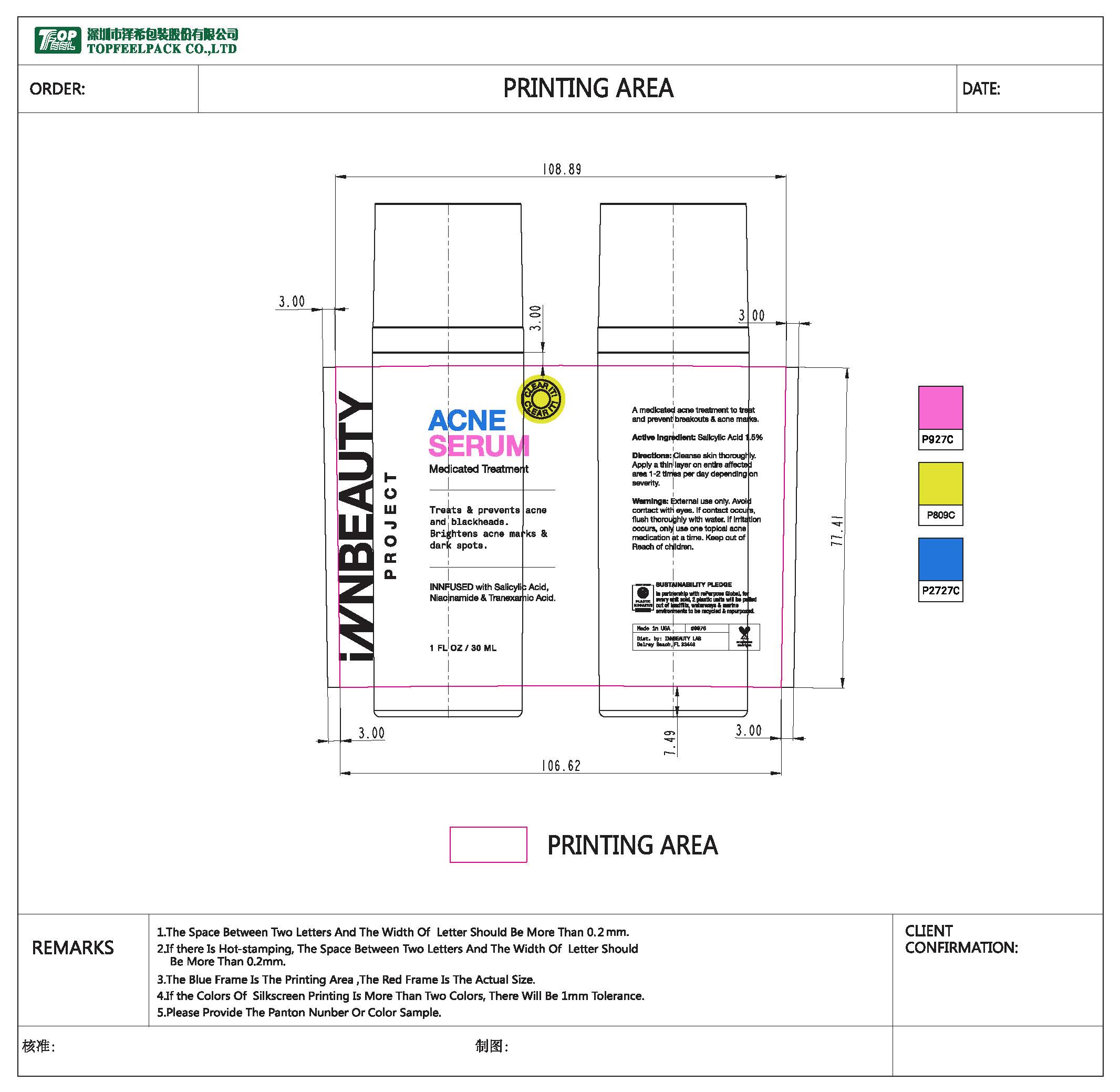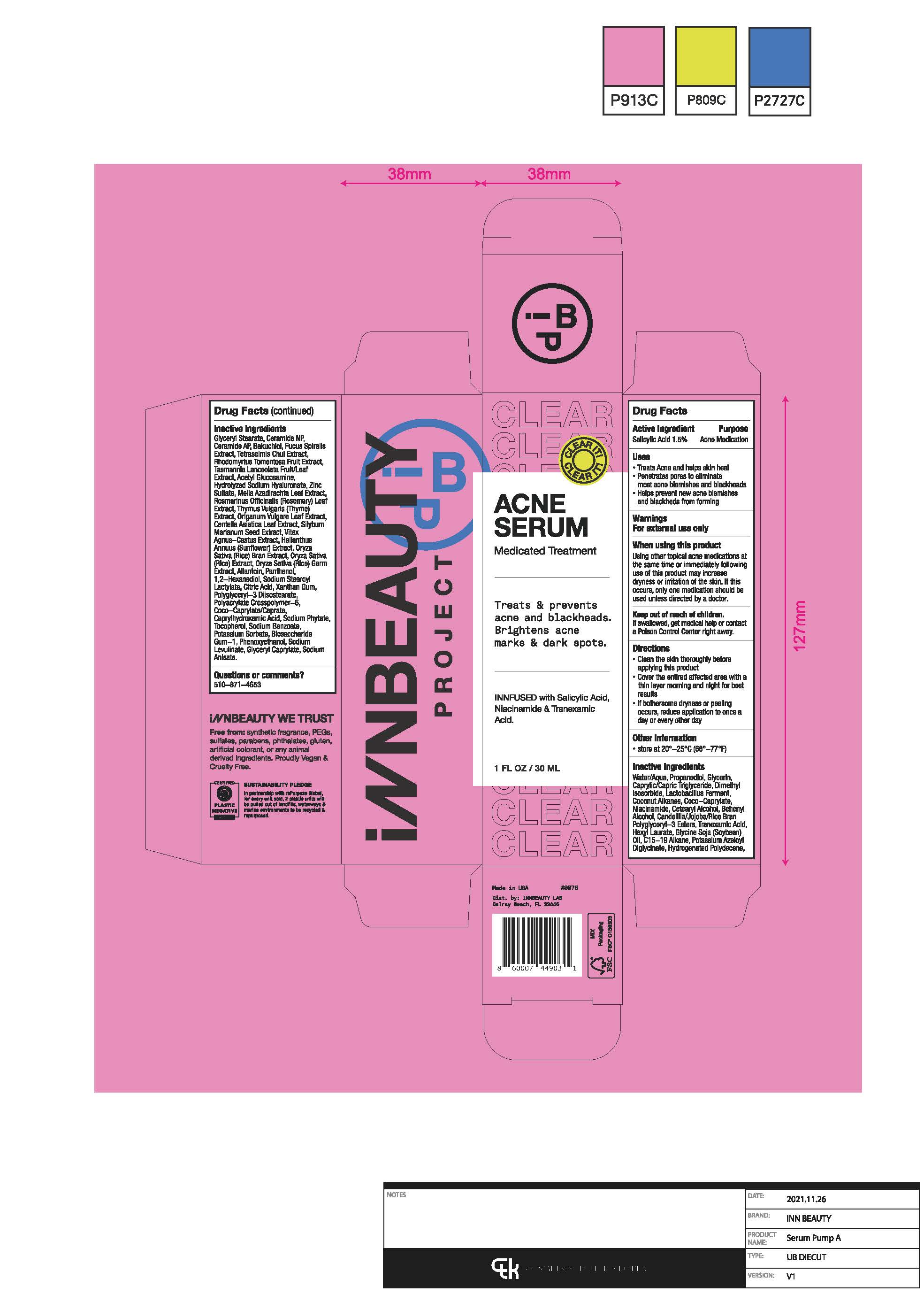 DRUG LABEL: cream
NDC: 61354-099 | Form: LOTION
Manufacturer: Oxygen Development LLC
Category: otc | Type: HUMAN OTC DRUG LABEL
Date: 20230626

ACTIVE INGREDIENTS: SALICYLIC ACID 1.5 mg/100 mg
INACTIVE INGREDIENTS: NIACINAMIDE 3 mg/100 mg; CETOSTEARYL ALCOHOL 2.5 mg/100 mg; C15-19 ALKANE 1.2 mg/100 mg; DIMETHYL ISOSORBIDE 4 mg/100 mg; COCONUT ALKANES 3.76 mg/100 mg; MEDIUM-CHAIN TRIGLYCERIDES 5.5 mg/100 mg; COCO-CAPRYLATE 3.5 mg/100 mg; LIMOSILACTOBACILLUS FERMENTUM 3.97 mg/100 mg; TRANEXAMIC ACID 2 mg/100 mg; BAKUCHIOL 0.5 mg/100 mg; POTASSIUM AZELOYL DIGLYCINATE 1 mg/100 mg; GLYCERIN 6.07 mg/100 mg; DOCOSANOL 2.5 mg/100 mg; SOYBEAN OIL 1.3 mg/100 mg; 1,2-HEXANEDIOL 0.75 mg/100 mg; SODIUM STEAROYL LACTYLATE 0.5 mg/100 mg; HEXYL LAURATE 1.5 mg/100 mg; GLYCERYL MONOSTEARATE 1 mg/100 mg; HYDROGENATED POLYDECENE TYPE I 1 mg/100 mg; CANDELILLA WAX 2.5 mg/100 mg; WATER 38.78 mg/100 mg; PROPANEDIOL 7.47 mg/100 mg

ACNE SERUM Medicated Treatment

Active Ingredient

Salicylic Acid

Purpose

Acne Medication

Uses

Treats Acne and helps skin heal. Penetrates pores to eliminate most acne blemishes and blackheads. Helps prevent new acne blemishes and blackheads from forming

Warnings

For external use only

When using use only

Using other topical acne medications at the same time or immediately following use of this product may increase dryness or irritation of the skin. If this occurs, only one medication should be used unless directed by a doctor.

Keep out of reach of children

If swallowed, get medical help or contact a Poison Control Center right away

Directions

Clean the skin thoroughly before applying this product.

Cover the entire affected area with a thin layer morning and night for best results.

If bothersome dryness or peeling occurs, reduce application to once a day or every other day.

Other information

Store at 20 - 25C (68-77F)

Inactive Ingredient

Water/Aqua, Propanediol, Glycerin, Caprylic/Capric Triglyceride, Dimethyl Isosorbide, Lactobacillus Ferment, Coconut Alkanes, Coco-Caprylate, Niacinamide, Candelilla/Jojoba/Rice Bran Polyglyceryl-3 Esters, Tranexamic Acid, Hexyl Laurate, Glycine Soja Soybean, C15-19 Alkane, Potassium Azeloyl Diglycinate, Hydrogenated Polydecene, Glyceryl Stearate, Ceramide NP, Ceramide AP, Bakuchiol, Fucus Spiralis Extract, Rhodomyrtus Tomentosa Fruit Extract, Tasmannia Lanceolata Fruit/Leaf Extract, Acetyl Glucosamine, Hydrolyzed Sodium Hyaluronate, Zinc Sulfate, Melia Azadirachta Leaf Extract, Centella Asiatica Leaf Extract, Silybum Marianum Seed Extract, Vitex Agnus - Castus Extra, Helianthus Annuus (Sunflower) Extract, Oryza Sativa (Rice) Bran Extract, Oryza Sativa (Rice) Extract, Oryza Sativa (Rice) Germ Extract, Allantoin, Panthenol, 1,2 - Hexanediol, Sodium Stearoyl Lactylate, Citric Acid, Xanthan Gum, Polyglyceryl - 3 Diisostearate, Polyacrylate Crosspolymer - 6, Coco - Caprylate/Caprate, Caprylhydroxamic Acid, Sodium Phytate, Tocopherol, Sodium Benzoate, Potassium Sorbate, Biosaccaharide Gum - 1, Phenoxyethanol, Sodium Anisate.